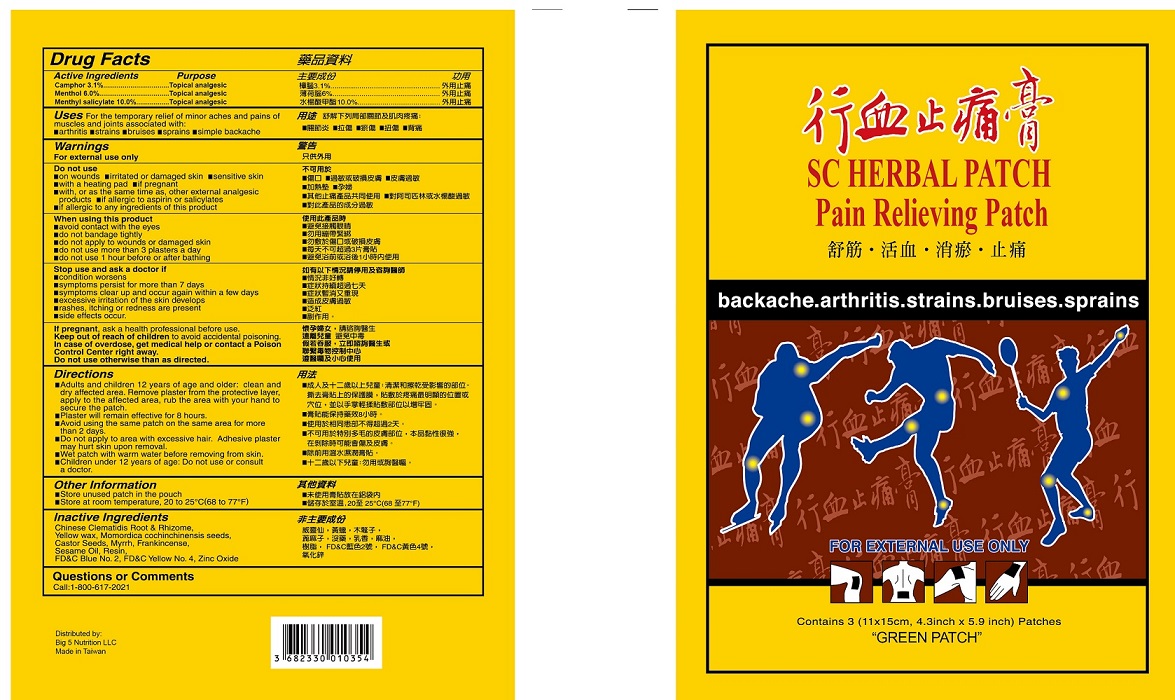 DRUG LABEL: SC HERBAL
NDC: 82198-0015 | Form: PATCH
Manufacturer: Big 5 Nutrition LLC
Category: otc | Type: HUMAN OTC DRUG LABEL
Date: 20231128

ACTIVE INGREDIENTS: MENTHOL, UNSPECIFIED FORM 0.06 g/1 g; METHYL SALICYLATE 0.1 g/1 g; CAMPHOR (SYNTHETIC) 0.031 g/1 g
INACTIVE INGREDIENTS: CLEMATIS CHINENSIS ROOT; INDIGOTINDISULFONATE SODIUM; MOMORDICA COCHINCHINENSIS SEED; MYRRH; FRANKINCENSE; PINUS MASSONIANA RESIN; RICINUS COMMUNIS SEED; SESAME OIL; FD&C YELLOW NO. 5; YELLOW WAX; ZINC OXIDE

SC Herbal Patch

Active Ingredients

Methyl Salicylate 10%

Menthol 6%

Camphor 3.1%

Purpose

External Analgesic

Uses

For the temporary relief of minor aches and pains of muscles and joints associated with: ■ arthritis ■ strains ■ bruises ■ sprains

■ simple backache

Warnings

For external use only

Do not use

■on wounds ■ irritated or damaged skin ■ sensitive skin ■ with a heating pad ■ if pregnant ■ with, or as the same time as, other external analgesic products ■ if allergic to aspirin or salicylates ■ if allergic to any ingredients of this product

When using this product

■ avoid contact wit the eyes

■ do not bandage tightly

■ do not apply to wounds or damaged skin

■ do not use more than 3 plasters a day

■ do not use 1 hour before or after bathing

Stop use and ask doctor if

■ condttion worsens

■ symptoms persist for more than 7 days

■ symptoms clear up and occur again wtthin a few days

■ excessive irritation of the skin develops

■ rashes, itching or redness are present

■ side effects occur.

PREGNANCY OR BREAST FEEDING

If pregnant,ask a health professional before use.

KEEP OUT OF REACH OF CHILDREN

Keep out of reach of childrento avoid accidental poisoning.

OVERDOSAGE

In case of overdose, get medical help or contact a Poison Control Center right away.

Do not use otherwise than as directed.

Directions

■ Adults and children 12 years of age and older: clean and dry affected area. Remove patch from the protective layer, apply to the affected area, rub the area with your hand to secure the patch.
■ Patch will remain effective for 8 hours.
■ Avoid using the same patch on the same area for more than 2 days.
■ Do not apply to area with excessive hair. Adhesive patch may hurt skin upon removal.
■ Wet patch with warm water before removing from skin
■ Children under 12 years of age: Do not use or consult a doctor.

Other information

■ store unused patch in the pouch
■ store at room temperature, 20 to 25°C(68 to 77°F)

Inactive ingredients

Chinese Clematidis Root & Rhizome, Yellow wax, Momordica cochinchinensis seeds, Castor Seeds, Myrrh, Frankincense, Sesame Oil, Resin, FD&C Blue No. 2, FD&C Yellow No. 4, Zinc Oxide

Questions or comments

Call: 1-800-617-2021